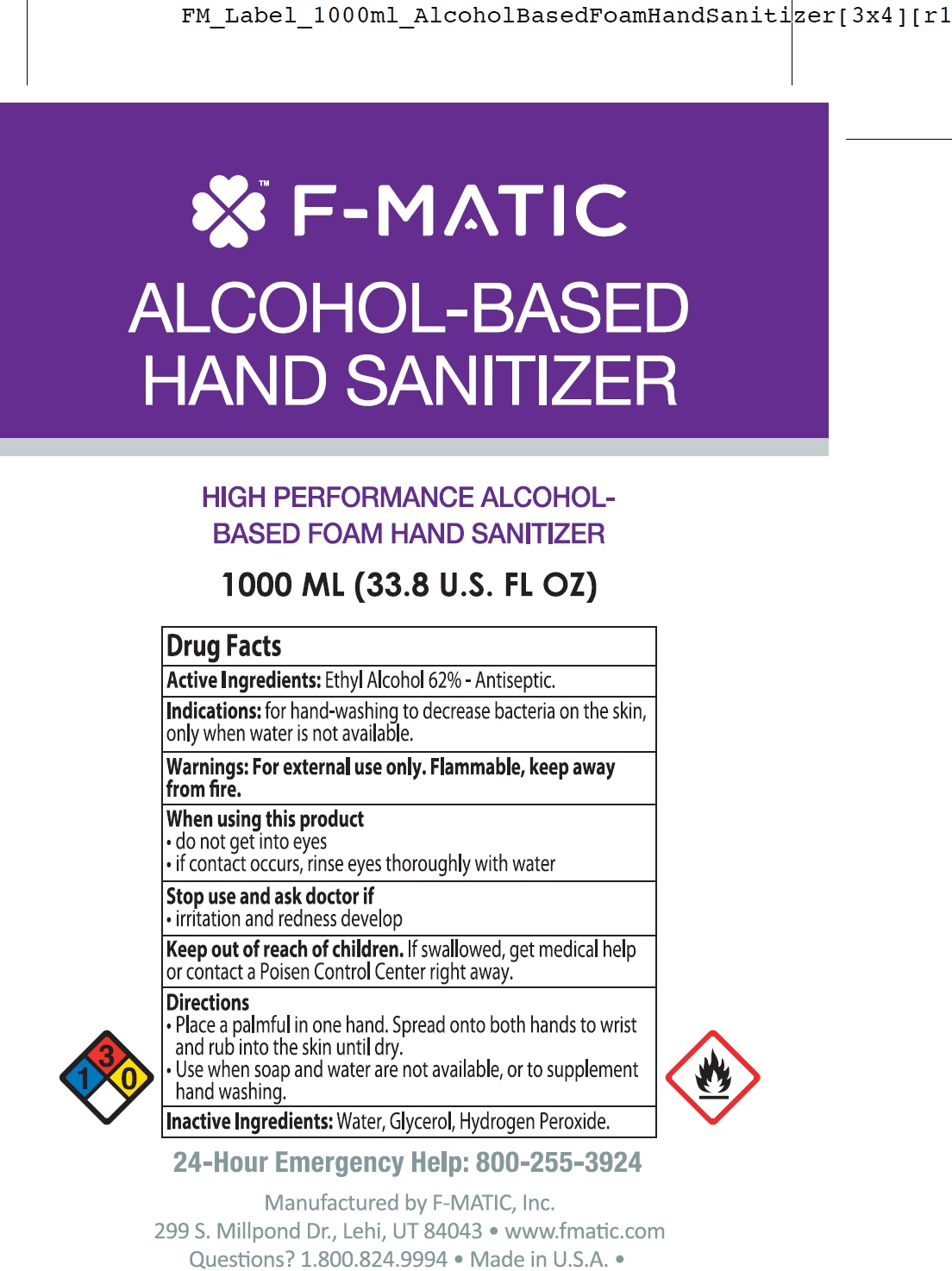 DRUG LABEL: F Matic Alcohol Based Hand Sanitizer
NDC: 77347-001 | Form: LIQUID
Manufacturer: F-Matic, Inc.
Category: otc | Type: HUMAN OTC DRUG LABEL
Date: 20200618

ACTIVE INGREDIENTS: ALCOHOL 0.62 mL/1 mL
INACTIVE INGREDIENTS: WATER; GLYCERIN; HYDROGEN PEROXIDE

F-Matic Alcohol-Based Hand Sanitizer

Active Ingredient:

Ethyl Alcohol 62%

PURPOSE

Antiseptic

Indications:

for hand-washing to decrease bacteria on the skin, only when water is not available.

Warnings:

For external use only. Flammable, keep away from fire.

When using this product

- do not get into eyes
- if contact occurs, rinse eyes thoroughly with water

Stop use and ask doctor if

irritation and redness develop

Keep out of reach of children.

If swallowed, get medical help or contact a Poison Control Center right away.

Directions

- Place a palmful in one hand. Spread onto both hands to wrist and rub into the skin until dry.
- Use when soap and water are not available, or to supplement hand washing.

Inactive Ingredients:

Water, Glycerol, Hydrogen Peroxide.